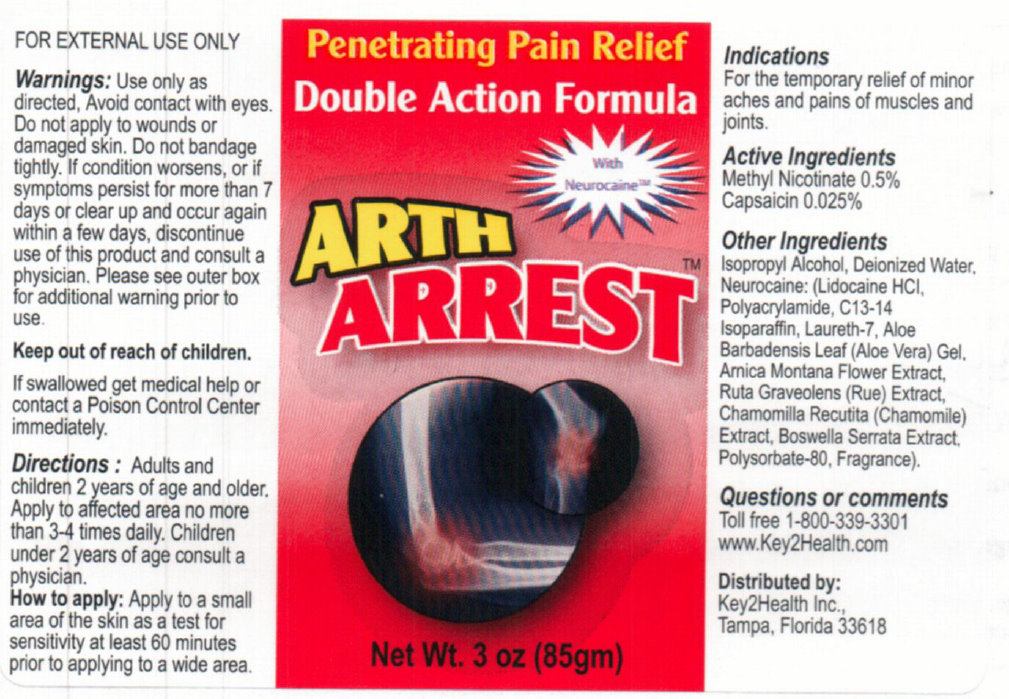 DRUG LABEL: Arth Arrest
NDC: 76018-100 | Form: CREAM
Manufacturer: Key 2 Health, Inc.
Category: otc | Type: HUMAN OTC DRUG LABEL
Date: 20231111

ACTIVE INGREDIENTS: METHYL NICOTINATE 0.5 g/100 g; CAPSAICIN 0.025 g/100 g
INACTIVE INGREDIENTS: ISOPROPYL ALCOHOL; WATER; LIDOCAINE HYDROCHLORIDE; POLYQUATERNIUM-7 (70/30 ACRYLAMIDE/DADMAC; 1600 KD); C13-14 ISOPARAFFIN; LAURETH-7; ALOE VERA LEAF; ARNICA MONTANA FLOWER; CHAMOMILE; POLYSORBATE 80

Arth Arrest

ACTIVE INGREDIENT

Active Ingredients Methyl Nicotinate 0.5% Capsaicin 0.025 %

PURPOSE

Indications For the temporary relief of minor aches and pains of muscles and joints.

WARNINGS

FOR EXTERNAL USE ONLY Warnings: Use only as directed, Avoid contact with eyes. Do not apply to wounds or damaged skin. Do not bandage tightly. If condition worsens, or if symptoms persists for more than 7 days or clear up and occur again within a few days, discontinue use of this product and consult a physician. Please see outer box for additional warnings prior to use.

Keep out of reach of children. If swallowed get medical help or contact a Poison Control Center immediately.

DOSAGE AND ADMINISTRATION

Directions: Adults and children 2 years of age and older. Apply to affected area no more than 3-4 times daily. Children under 2 years of age consult a physician.

INDICATIONS AND USAGE

How to apply: Apply to a small area of the skin as a test for sensitivity at least 60 minutes prior to applying to a wide area.

INACTIVE INGREDIENT

Other Ingredients

Isopropyl Alcohol, Deionized Water, Neurocaine:(Lidocaine HCl, Polyacrylamide, C13-14 Isoparaffin, Laureth-7, Aloe Barbadensis Leaf (Aloe Vera) Gel, Arnica Montana Flower Extract, Ruta Graveolens (Rue) Extract, Chamomilla Recutita (Chamomile) Extract, Boswella Serrata Extract, Polysorbate-80, Fragrance).

Questions or comments Toll free 1-800-339-3301 www.Key2Health.com

Distributed by: Key2Health Inc., Tampa, Florida 33618

PACKAGE LABEL

Penetrating Pain Relief

Double Action Formula

With Neurocaine

ARTH ARREST

Net Wt. 3 oz (85gm)